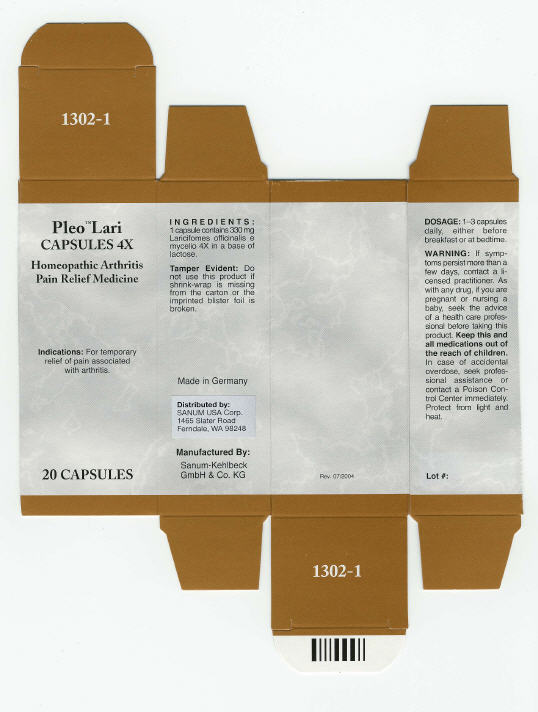 DRUG LABEL: Pleo Lari
NDC: 60681-1302 | Form: CAPSULE
Manufacturer: Sanum Kehlbeck GmbH & Co. KG
Category: homeopathic | Type: HUMAN OTC DRUG LABEL
Date: 20100106

ACTIVE INGREDIENTS: laricifomes officinalis fruiting body 4 [hp_X]/1 1
INACTIVE INGREDIENTS: lactose

Pleo™ Lari
CAPSULES 4X

Homeopathic Arthritis Pain Relief Medicine

20 CAPSULES

Indications

For temporary relief of pain associated with arthritis.

INGREDIENTS

1 capsule contains 330 mg Laricifomes officinalis e mycelio 4X in a base of lactose.

Tamper Evident

Do not use this product if shrink-wrap is missing from the carton or the imprinted blister foil is broken.

DOSAGE

1–3 capsules daily, either before breakfast or at bedtime.

WARNING

If symptoms persist more than a few days, contact a licensed practitioner. As with any drug, if you are pregnant or nursing a baby, seek the advice of a health care professional before taking this product.

KEEP OUT OF REACH OF CHILDREN

Keep this and all medications out of the reach of children. In case of accidental overdose, seek professional assistance or contact a Poison Control Center immediately.

STORAGE AND HANDLING

Protect from light and heat.

Made in Germany

Distributed by:
SANUM USA Corp.
1465 Slater Road
Ferndale, WA 98248

Manufactured By:
Sanum-Kehlbeck
GmbH & Co. KG

Rev. 07/2004

PRINCIPAL DISPLAY PANEL - 20 Capsule Carton

Pleo™ Lari
CAPSULES 4X

Homeopathic Arthritis
Pain Relief Medicine

Indications: For temporary
relief of pain associated
with arthritis.

20 CAPSULES